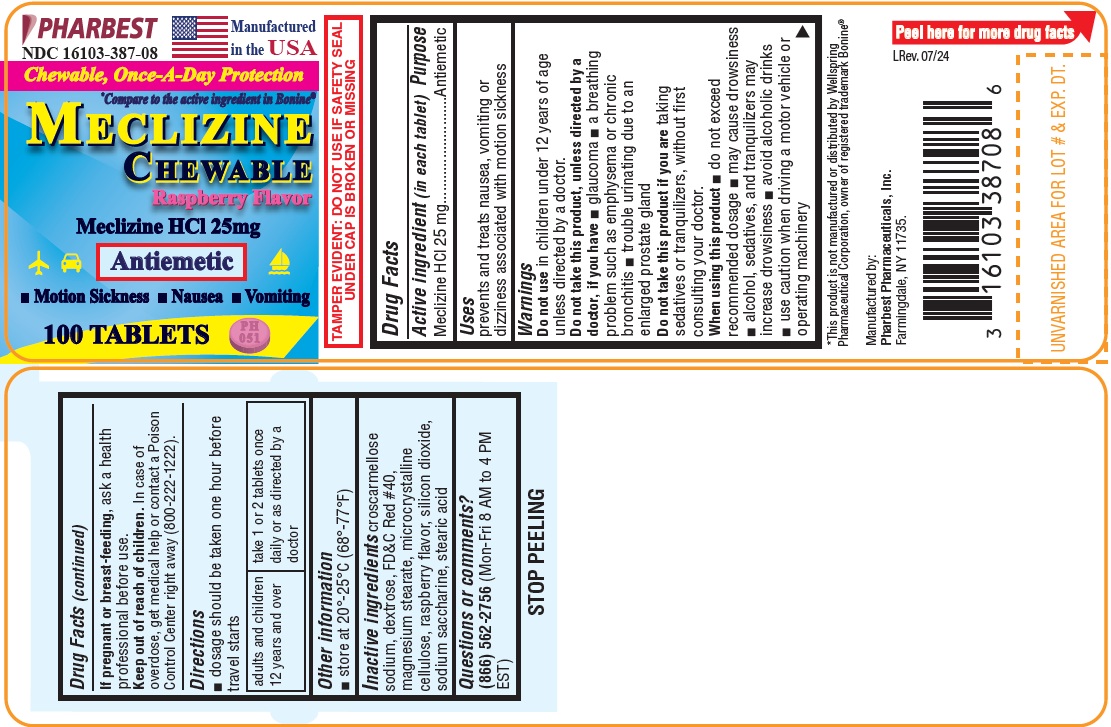 DRUG LABEL: MECLIZINE
NDC: 16103-387 | Form: TABLET, CHEWABLE
Manufacturer: Pharbest Pharmaceuticals, Inc.
Category: otc | Type: HUMAN OTC DRUG LABEL
Date: 20251224

ACTIVE INGREDIENTS: MECLIZINE HYDROCHLORIDE 25 mg/1 1
INACTIVE INGREDIENTS: CROSCARMELLOSE SODIUM; DEXTROSE; FD&C RED NO. 40; MAGNESIUM STEARATE; CELLULOSE, MICROCRYSTALLINE; SILICON DIOXIDE; SACCHARIN SODIUM; STEARIC ACID; RASPBERRY

Drug Facts

Active ingredient (in each tablet)

Meclizine HCl 25mg

Purpose

Antiemetic

Uses

prevents and treats nausea, vomiting or dizziness associated with motion sickness

Warnings

Do not use in children under 12 years of age unless directed by a doctor.

Do not take this product unless directed by a doctor, if you have

- glaucoma
- a breathing problem such as emphysema or chronic bronchitis
- trouble urinating due to an enlarged prostate gland

Do not take this product if you are taking sedatives or tranquilizers, without first consulting your doctor.

When using this product

- do not exceed recommended dosage
- may cause drowsiness
- alcohol, sedatives, and tranquilizers may increase drowsiness
- avoid alcoholic drinks
- use caution when driving a motor vehicle or operating machinery

If pregnant or breast-feeding,

ask a health professional before use.

Keep out of reach of children.

In case of overdose, get medical help or contact a Poison Control Center right away (800-222-1222)

Directions

- doage should be taken one hour before travel starts

Adults and children 12 years and over | take 1 or 2 tablets once daily or as directed by doctor

Other information

- Tamper Evident: do not use if safety seal under cap is broken or missing
- store at 20°-25°C (68°-77°F)

Inactive ingredients

Croscarmellose sodium, dextrose, FD&C Red#40, raspberry flavor, magnesium stearate, microcrystalline cellulose, silicon dioxide, sodium saccharine, stearic acid

Questions or comments?

(866) 562-2756 (Mon-Fri, 8 AM - 4 PM EST)

PACKAGE LABEL

PHARBEST

NDC 16103-387-08

Manufactured in the USA

Chewable, Once-A-Day Protection

*Compare to the active ingredient in Bonine®

MECLIZINE

CHEWABLE

Raspberry Flavor

Meclizine HCl 25mg

Antiemetic

• Motion Sickness • Nausea • Vomiting

100 TABLETS